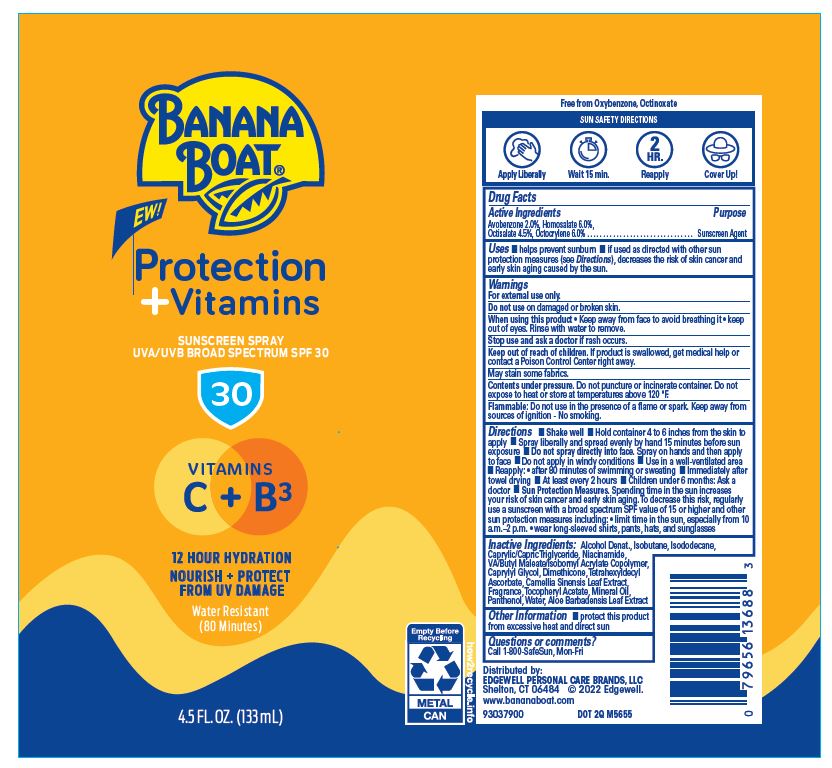 DRUG LABEL: BANANA BOAT PROTECTION PLUS VITAMINS SUNSCREEN UVA/UVB BORAD SPECTRUM SPF 30
NDC: 63354-641 | Form: AEROSOL, SPRAY
Manufacturer: Edgewell Personal Care Brands LLC
Category: otc | Type: HUMAN OTC DRUG LABEL
Date: 20241027

ACTIVE INGREDIENTS: AVOBENZONE 2 g/100 g; OCTISALATE 4.5 g/100 g; HOMOSALATE 6 g/100 g; OCTOCRYLENE 6 g/100 g
INACTIVE INGREDIENTS: ISOBUTANE; CAPRYLYL GLYCOL; DIMETHICONE; .ALPHA.-TOCOPHEROL ACETATE; PANTHENOL; ALOE VERA LEAF; ISODODECANE; TETRAHEXYLDECYL ASCORBATE; GREEN TEA LEAF; MINERAL OIL; WATER; DEHYDRATED ALCOHOL; NIACINAMIDE

Active Ingredients

Avobenzone 2.0%, Homosalate 6.0%, Octisalate 4.5%, Octocrylene 6.0%

Purpose

Sunscreen Agent

Uses

• helps prevent sunburn • if used as directed with other sun protection measures (see Directions), decreases the risk of skin cancer and early skin aging caused by the sun.

Warnings

For external use only.

May stain some fabrics.

Contents under pressure. Do not puncture or incinerate container. Do not expose to heat or store at temperatures above 120 °F.

Flammable: Do not use in the presence of a flame or spark. Keep away from sources of ignition - No smoking.

Do not use

on damaged or broken skin.

When using this product

Keep away from face to avoid breathing it • keep out of eyes. Rinse with water to remove

Stop use and ask a doctor

if rash occurs.

Keep out of reach of children.

If product is swallowed, get medical help or contact a Poison Control Center right away

Directions

• Shake well • Hold container 4 to 6 inches from the skin to apply • Spray liberally and spread evenly by hand 15 minutes before sun
exposure • Do not spray directly into face. Spray on hands and then apply to face • Do not apply in windy conditions • Use in a well-ventilated area • Reapply: • after 80 minutes of swimming or sweating • Immediately after towel drying • At least every 2 hours • Children under 6 months: Ask a doctor • Sun Protection Measures. Spending time in the sun increases your risk of skin cancer and early skin aging. To decrease this risk, regularly use a sunscreen with a broad spectrum SPF value of 15 or higher and other
sun protection measures including: • limit time in the sun, especially from 10 a.m.–2 p.m. • wear long-sleeved shirts, pants, hats, and sunglasses

Inactive Ingredients

Alcohol Denat., Isobutane, Isododecane, Caprylic/Capric Triglyceride, Niacinamide, VA/Butyl Maleate/Isobornyl Acrylate Copolymer, Caprylyl Glycol, Dimethicone,Tetrahexyldecyl Ascorbate, Camellia Sinensis Leaf Extract, Fragrance,Tocopheryl Acetate, Mineral Oil, Panthenol,Water, Aloe Barbadensis Leaf Extract

Other Information

protect this product from excessive heat and direct sun

Questions or comments?

Call 1-800-SafeSun, Mon-Fri

PRINCIPAL DISPLAY PANEL

BANANA

BOAT

NEW!

Protection

+ Vitamins

SUNSCREEN SPRAY

UVA/UVB BROAD SPECTRUM SPF 30

30

VITAMINS

C + B3

12 HOUR HYDRATION
NOURISH + PROTECT
FROM UV DAMAGE

Water Resistant
(80 Minutes)

4.5 FL.OZ. (133 mL)